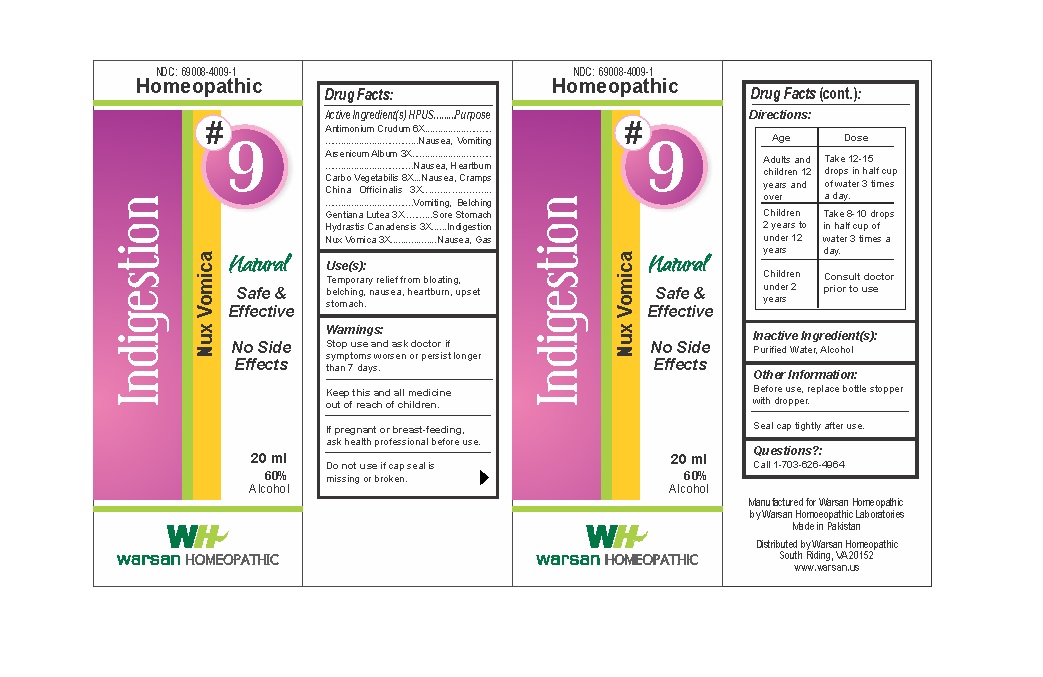 DRUG LABEL: Combination Remedy 9 - Indigestion
NDC: 69008-4009 | Form: SOLUTION/ DROPS
Manufacturer: Warsan Homoeopathic Laboratories
Category: homeopathic | Type: HUMAN OTC DRUG LABEL
Date: 20171225

ACTIVE INGREDIENTS: ANTIMONY TRISULFIDE 6 [hp_X]/1 mL; ARSENIC TRIOXIDE 3 [hp_X]/1 mL; ACTIVATED CHARCOAL 8 [hp_X]/1 mL; GENTIANA LUTEA ROOT 3 [hp_X]/1 mL; GOLDENSEAL 3 [hp_X]/1 mL; STRYCHNOS NUX-VOMICA SEED 3 [hp_X]/1 mL; CINCHONA OFFICINALIS BARK 3 [hp_X]/1 mL
INACTIVE INGREDIENTS: ALCOHOL; WATER

Keep out of reach of children.

ACTIVE INGREDIENT

Antimonium Crudum 6X

Arsenicum Album 3X

Carbo Vegetabilis 8X

China Officinalis 3X

Gentiana Lutea 3X

Hydrastis Canadensis 3X

Nux Vomica 3X

PURPOSE

Temporary relief from bloating, belching, nausea, heartburn, upset stomach.

Stop use and ask doctor if symptoms worsen or persist longer than 7 days.

If pregnant or breast-feeding, ask health professional before use.

Do not use if tamper evident seal is missing or broken.

INACTIVE INGREDIENT

Purified Water

Alcohol

DOSAGE AND ADMINISTRATION

Adults and children 12 years and older: Take 10-15 drops in half cup of water 3 times a day.

Children 2 years to under 12 years: Take 8-10 drops in half cup of water of 3 times a day.

Children under 2 years: Consult doctor prior to use.

INDICATIONS AND USAGE

Temporary relief from bloating, belching, nausea, heartburn, upset stomach.